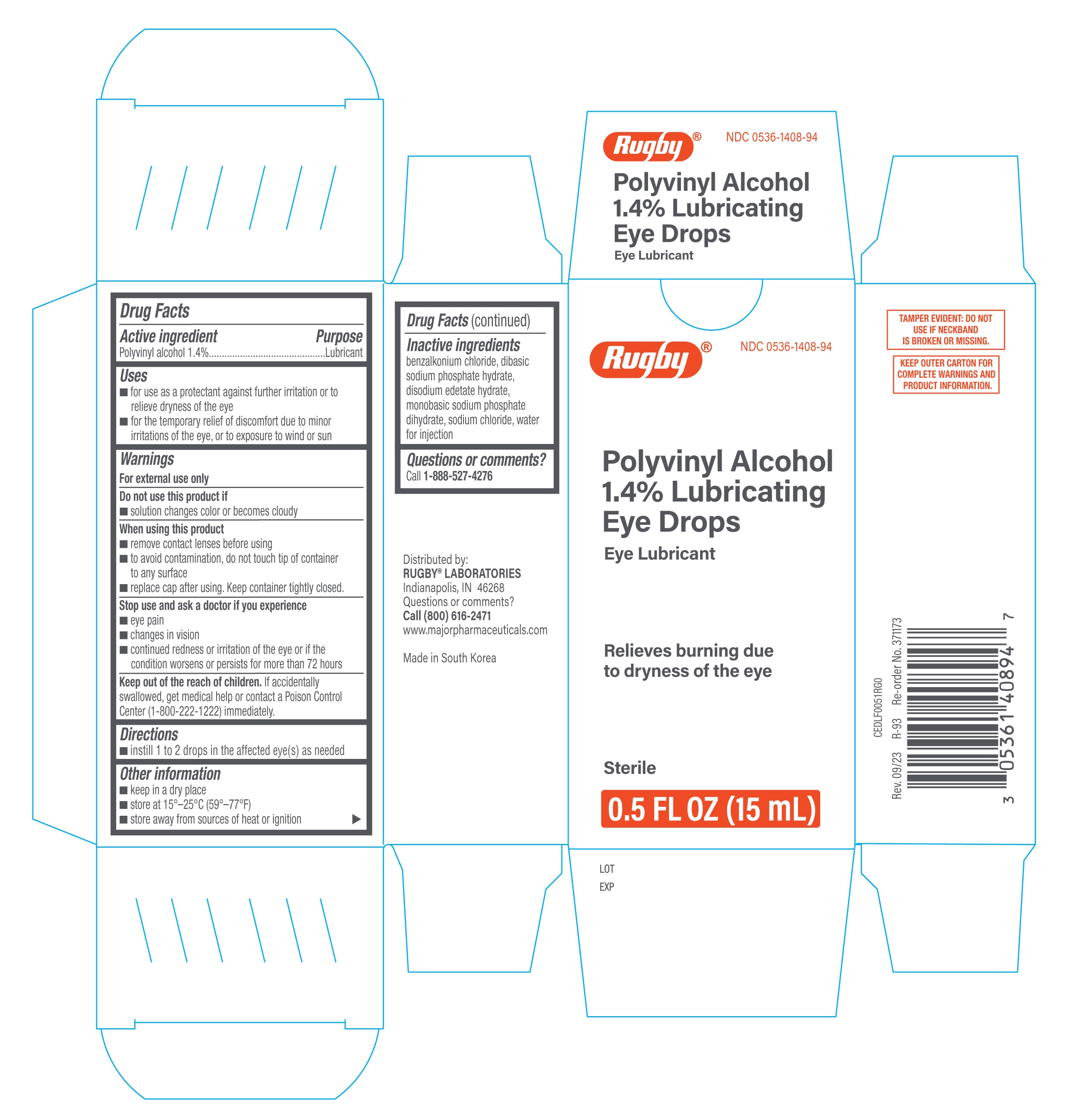 DRUG LABEL: Rugby Polyvinyl Alcohol 1.4% Lubricating Eye Drops
NDC: 0536-1408 | Form: SOLUTION/ DROPS
Manufacturer: Rugby Laboratories
Category: otc | Type: HUMAN OTC DRUG LABEL
Date: 20251230

ACTIVE INGREDIENTS: POLYVINYL ALCOHOL, UNSPECIFIED 1.4 g/100 mL
INACTIVE INGREDIENTS: SODIUM PHOSPHATE, DIBASIC, DODECAHYDRATE; WATER; BENZALKONIUM CHLORIDE; EDETATE DISODIUM; SODIUM PHOSPHATE, MONOBASIC, DIHYDRATE; SODIUM CHLORIDE

Rugby Polyvinyl Alcohol 1.4% Lubricating Eye Drops 15mL (PLD)

Active ingredient

Polyvinyl alcohol 1.4%

Purpose

Lubricant

Uses

- for use as a protectant against further irritation or to relieve dryness of the eye
- for the temporary relief of discomfort due to minor irritations of the eye, or to exposure to wind or sun

Warnings

For external use only

Do not use this product if

- solution changes color or becomes cloudy

When using this product

- remove contact lenses before using
- to avoid contamination, do not touch tip of container to any surface
- replace cap after using. Keep container tightly closed.

Stop use and ask a doctor if you experience

- eye pain
- changes in vision
- continued redness or irritation of the eye or if the condition worsens or persists for more than 72 hours

Keep out of the reach of children.

If accidentally swallowed, get medical help or contact a Poison Control Center (1-800-222-1222) immediately.

Directions

- instill 1 to 2 drops in the affected eye(s) as needed

Other information

- keep in a dry place
- store at 15°-25°C (59°-77°F)
- store away from sources of heat or ignition

Inactive ingredients

benzalkonium chloride, dibasic sodium phosphate hydrate, disodium edetate hydrate, monobasic sodium phosphate dihydrate, sodium chloride, water for injection.